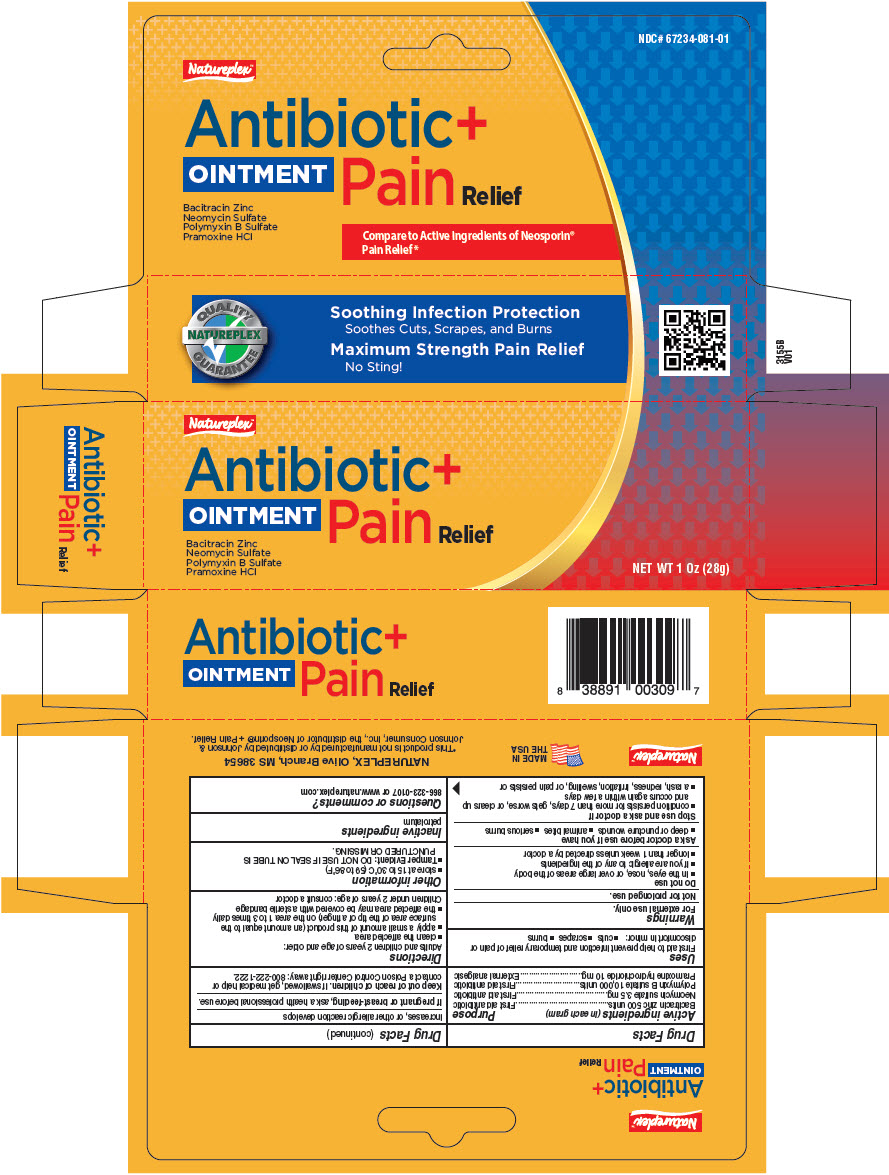 DRUG LABEL: Natureplex Antibiotic plus Pain
NDC: 67234-081 | Form: OINTMENT
Manufacturer: Natureplex, LLC
Category: otc | Type: HUMAN OTC DRUG LABEL
Date: 20260129

ACTIVE INGREDIENTS: BACITRACIN ZINC 500 [iU]/1 g; NEOMYCIN SULFATE 3.5 mg/1 g; POLYMYXIN B SULFATE 10000 [iU]/1 g; PRAMOXINE HYDROCHLORIDE 10 mg/1 g
INACTIVE INGREDIENTS: PETROLATUM

Natureplex™ Antibiotic Ointment + Pain
Topical

Drug Facts

ACTIVE INGREDIENT

Active ingredients (in each gram) | Purpose
Bacitracin zinc 500 units | First aid antibiotic
Neomycin sulfate 3.5 mg | First aid antibiotic
Polymyxin B sulfate 10,000 units | First aid antibiotic
Pramoxine hydrochloride 10 mg | External analgesic

Uses

First aid to help prevent infection and temporary relief of pain or discomfort in minor:

- cuts
- scrapes
- burns

Warnings

For external use only.

Not for prolonged use.

Do not use

- in the eyes, nose, or over large areas of the body
- if you are allergic to any of the ingredients
- longer than 1 week unless directed by a doctor

Ask a doctor before use if you have

- deep or puncture wounds
- animal bites
- serious burns

Stop use and ask a doctor if

- condition persists for more than 7 days, gets worse, or clears up and occurs again within a few days
- a rash, redness, irritation, swelling, or pain persists or increases, or other allergic reaction develops

PREGNANCY OR BREAST FEEDING

If pregnant or breast-feeding, ask a health professional before use.

Keep out of reach of children. If swallowed, get medical help or contact a Poison Control Center right away: 800-222-1222.

Directions

Adults and children 2 years of age and older:

- clean the affected area
- apply a small amount of this product (an amount equal to the surface area of the tip of a finger) on the area 1 to 3 times daily
- the affected area may be covered with a sterile bandage

Children under 2 years of age: consult a doctor

Other information

- store at 15 to 30°C (59 to 86°F)
- Tamper Evident: DO NOT USE IF SEAL ON TUBE IS PUNCTURED OR MISSING.

Inactive ingredients

petrolatum

Questions or comments?

866-323-0107 or www.natureplex.com

PRINCIPAL DISPLAY PANEL - 28 g Tube Carton

Natureplex™

Antibiotic+
OINTMENT
Pain Relief

Bacitracin Zinc
Neomycin Sulfate
Polymyxin B Sulfate
Pramoxine HCl

NET WT 1 Oz (28g)